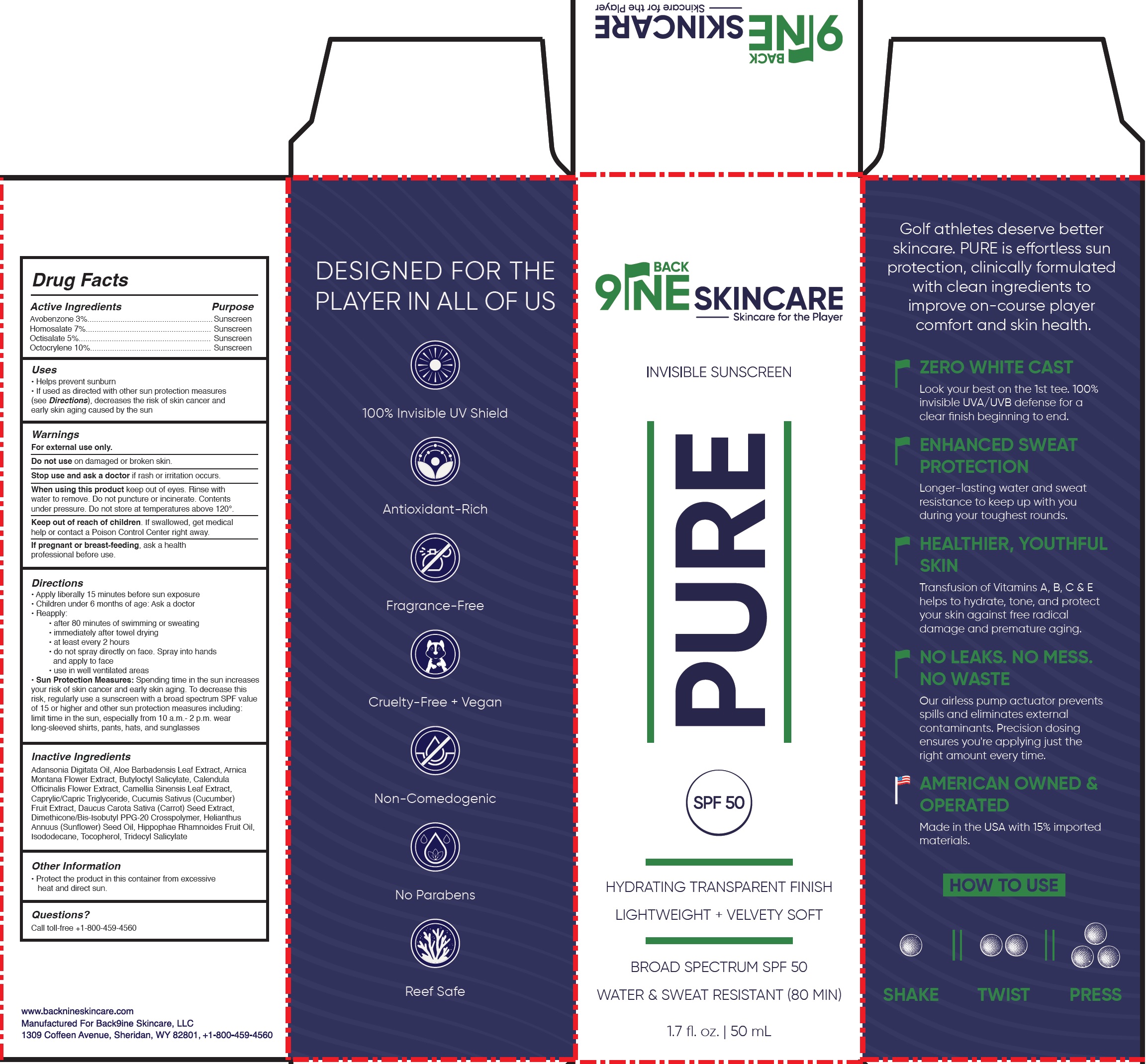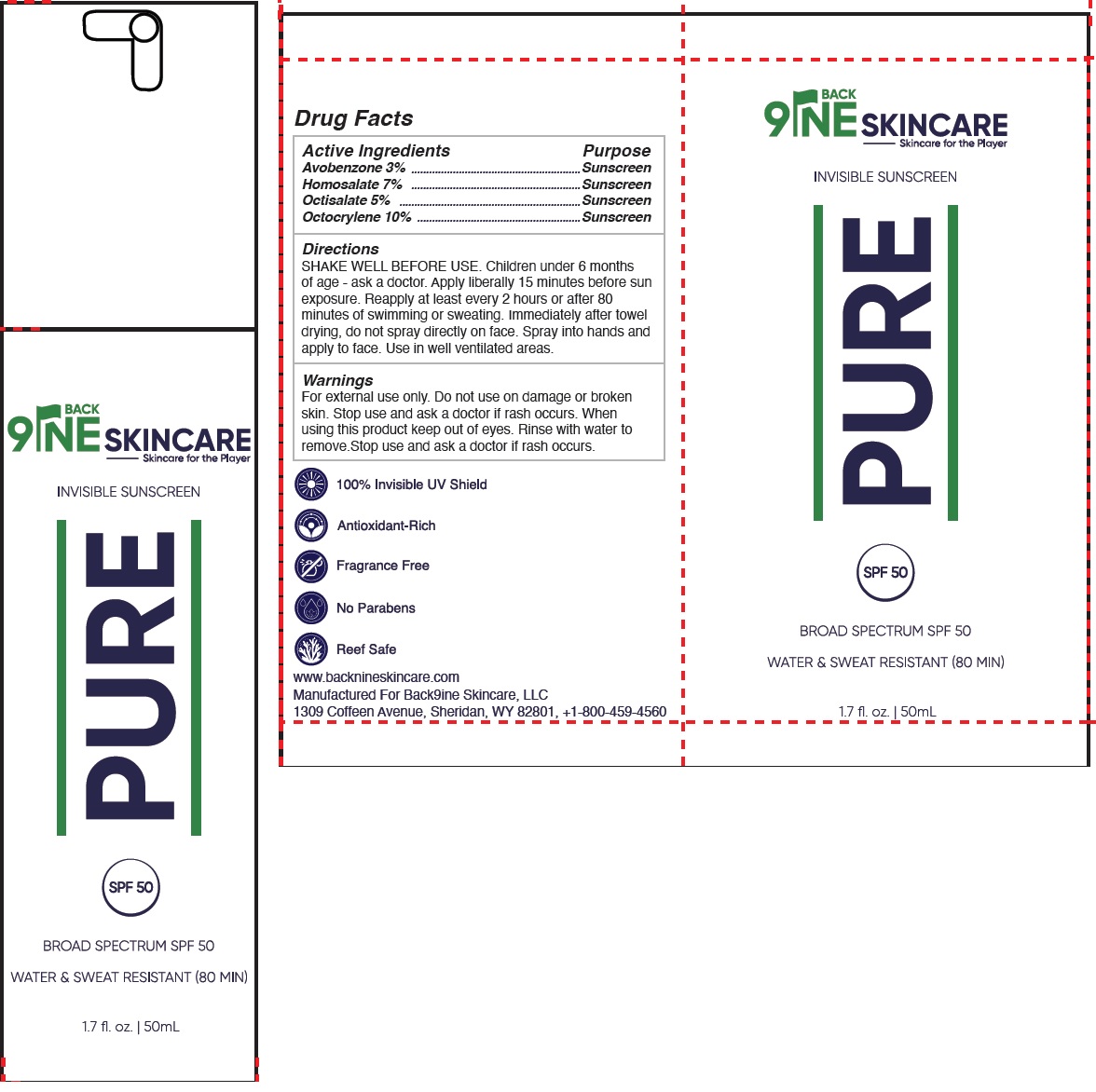 DRUG LABEL: Back9ine Skincare Pure Invisible Sunscreen SPF 50
NDC: 85536-585 | Form: GEL
Manufacturer: Back 9ine Skincare, LLC
Category: otc | Type: HUMAN OTC DRUG LABEL
Date: 20250422

ACTIVE INGREDIENTS: AVOBENZONE 30 mg/1 mL; HOMOSALATE 70 mg/1 mL; OCTISALATE 50 mg/1 mL; OCTOCRYLENE 100 mg/1 mL
INACTIVE INGREDIENTS: ADANSONIA DIGITATA SEED OIL; ALOE VERA LEAF; ARNICA MONTANA FLOWER; BUTYLOCTYL SALICYLATE; CALENDULA OFFICINALIS FLOWER; GREEN TEA LEAF; MEDIUM-CHAIN TRIGLYCERIDES; CUCUMBER; DAUCUS CAROTA SUBSP. SATIVUS SEED; DIMETHICONE/BIS-ISOBUTYL PPG-20 CROSSPOLYMER; SUNFLOWER OIL; HIPPOPHAE RHAMNOIDES FRUIT OIL; ISODODECANE; TOCOPHEROL; TRIDECYL SALICYLATE

Back9ine Skincare Pure Invisible Sunscreen SPF 50

Active Ingredients

Avobenzone 3%
Homosalate 7%
Octisalate 5%
Octocrylene 10%

Purpose

Sunscreen

Uses

- Helps prevent sunburn
- If used as directed with other sun protection measures (see Directions), decreases the risk of skin cancer and early skin aging caused by the sun

Warnings

For external use only.

Do not use

on damaged or broken skin.

Stop use and ask a doctor if

if rash or irritation occurs.

When using this product

keep out of eyes. Rinse with water to remove. Do not puncture or incinerate. Contents under pressure. Do not store at temperatures above 120°.

Keep out of reach of children.

If swallowed, get medical help or contact a Poison Control Center right away.

If pregnant or breast-feeding,

ask a health professional before use.

Directions

- Apply liberally 15 minutes before sun exposure
- Children under 6 months of age: Ask a doctor
- Reapply:
  • after 80 minutes of swimming or sweating
  • immediately after towel drying
  • at least every 2 hours
  • do not spray directly on face. Spray into hands and apply to face
  • use in well ventilated areas
- Sun Protection Measures:Spending time in the sun increases your risk of skin cancer and early skin aging. To decrease this risk, regularly use a sunscreen with a broad spectrum SPF value of 15 or higher and other sun protection measures including: limit time in the sun, especially from 10 a.m.- 2 p.m. wear long-sleeved shirts, pants, hats, and sunglasses

Inactive Ingredients

Adansonia Digitata Oil, Aloe Barbadensis Leaf Extract, Arnica Montana Flower Extract, Butyloctyl Salicylate, Calendula Officinalis Flower Extract, Camellia Sinensis Leaf Extract, Caprylic/Capric Triglyceride, Cucumis Sativus (Cucumber) Fruit Extract, Daucus Carota Sativa (Carrot) Seed Extract, Dimethicone/Bis-Isobutyl PPG-20 Crosspolymer, Helianthus Annuus (Sunflower) Seed Oil, Hippophae Rhamnoides Fruit Oil, Isododecane, Tocopherol, Tridecyl Salicylate

Other Information

- Protect the product in this container from excessive heat and direct sun.

Questions?

Call toll-free +1-800-459-4560